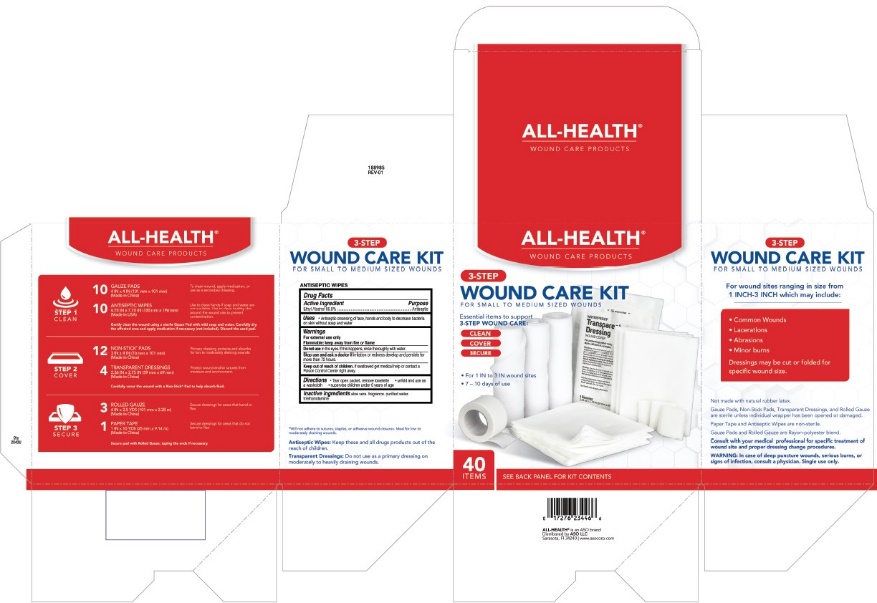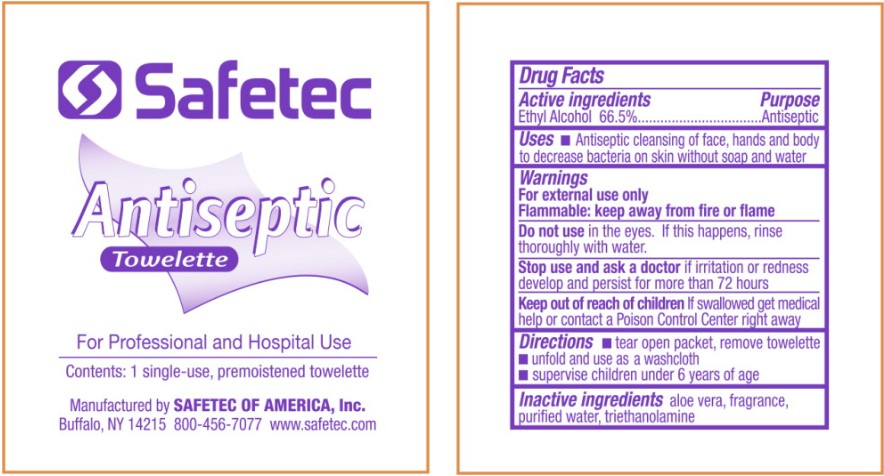 DRUG LABEL: All-Health Wound Care Kit
NDC: 51142-003 | Form: KIT | Route: TOPICAL
Manufacturer: ASO LLC
Category: otc | Type: HUMAN OTC DRUG LABEL
Date: 20240820

ACTIVE INGREDIENTS: ALCOHOL 665 mL/1 L
INACTIVE INGREDIENTS: ALOE VERA LEAF; WATER; TROLAMINE

ALL-HEALTH WOUND CARE KIT

Contents – All-Health Wound Care Kit

ALL-HEALTH®

WOUND CARE PRODUCTS
STEP 1 CLEAN
10 GAUZE PADS To clean wound, apply medication, or use a secondary dressing.
4 IN x 4 IN (101 mm x 101 mm)
(Made in China)
10 ANTISEPTIC WIPES Use to clean hands if soap and water are not available. Use to
4.75 IN x 7.75 IN (120 mm x 196 mm)clean healthy skin around the wound site to prevent contamination.
(Made in USA)
Gently clean the wound using a sterile Gauze Pad with mild soap and water. Carefully dry the affected area and apply medication if necessary (not included). Discard the used pad.
STEP 2 COVER
12 NON-STICK* PADS Primary dressing protects and absorbs for low to moderately
3 IN x 4 IN (76 mm x 101 mm) draining wounds.
(Made in China)
4 TRANSPARENT DRESSINGS Protect wound and/or sutures from moisture and environment.
2.36 IN x 2.75 IN (59 mm x 69 mm)
(Made in China)
Carefully cover the wound with a Non-Stick* Pad to help absorb fluid.
STEP 3 SECURE
3 ROLLED GAUZE Secure dressings for areas that bend or flex.
4 IN x 2.5 YDS (101 mm x 2.28 m)
(Made in China)
1 PAPER TAPE Secure dressings for areas that do not bend or flex.
1 IN x 10 YDS (25 mm x 9.14 m)
(Made in China)
Secure pad with Rolled Gauze, taping the ends if necessary.
*Will not adhere to sutures, staples, or adhesive wound closures. Ideal for low to moderately draining wound.

Antiseptic Wipes: Keep these and all drugs products out of the reach of children.

Transparent Dressings: Do not use as a primary dressing on moderately to heavily draining wounds.

Other Safety Information – All-Health Wound Care Kit

3-STEP
WOUND CARE KIT
FOR SMALL TO MEDIUM SIZED WOUNDS
For wound sites ranging in size from
1 INCH - 3 INCH which may include:

- Common Wounds
- Lacerations
- Abrasions
- Minor burns
  Dressings may be cut or folded for specific wound size.

Not made with natural rubber latex.
Gauze Pads, Non-Stick Pads, Transparent Dressings, and Rolled Gauze are sterile unless individual wrapper has been opened or damaged.
Paper Tape and Antiseptic Wipes are non-sterile.
Gauze Pads and Rolled Gauze are Rayon-polyester bend.

Consult with your medical professional for specific treatment of wound site and proper dressing change procedures.

WARNING: In case of deep puncture wounds, serious burns, or signs of infection, consult a physician. Single use only.

Active ingredients – Antiseptic Wipes

Ethyl Alcohol 66.5%

Purpose – Antiseptic Wipes

Antiseptic

Uses – Antiseptic Wipes

- Antiseptic cleansing of face, hands and body to decrease bacteria on skin without soap and water

Warnings – Antiseptic Wipes

For external use only
Flammable: keep away from fire or flame

Do not use – Antiseptic Wipes

in the eyes. If this happens, rinse thoroughly with water.

Stop use and ask a doctor – Antiseptic Wipes

if irritation or redness develop and persists for more than 72 hours

Keep out of reach of children – Antiseptic Wipes

If swallowed get medical help or contact a Poison Control Center right away

Directions – Antiseptic Wipes

- tear open packet, remove towelette
- unfold and use as a washcloth
- supervise children under 6 years of age

Inactive ingredients – Antiseptic Wipes

aloe vera, fragrance, purified water, triethanolamine

Principal Display Panel – All-Health Wound Care Kit

ALL-HEALTH®
WOUND CARE PRODUCTS
3-STEP
WOUND CARE KIT
FOR SMALL TO MEDIUM SIZED WOUNDS
Essential items to support
3-STEP WOUND CARE:
CLEAN
COVER
SECURE

- For 1 IN to 3 IN wound sites
- 7 – 10 days of use

40 ITEMS
SEE BACK PANEL FOR KIT CONTENTS
ALL-HEALTH®is an ASO brand
Distributed by ASO LLC
Sarasota, Fl 34240 | www.asocorp.com

Label

Principal Display Panel – Antiseptic Wipes

Safetec

Antiseptic
Towelette

For Professional and Hospital Use
Contents: 1 single-use, premoistened towelette
Manufactured by SAFETEC OF AMERICA, Inc.
Buffalo, NY 14215 800-456-7077 www.safetec.com

Label